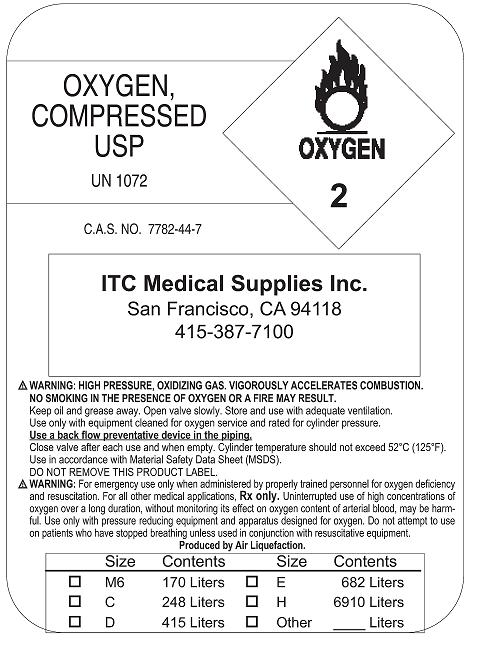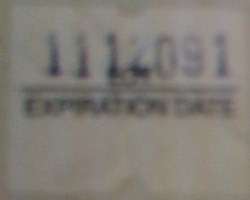 DRUG LABEL: Oxygen
NDC: 42209-1995 | Form: GAS
Manufacturer: ITC  Medical Supplies
Category: prescription | Type: HUMAN PRESCRIPTION DRUG LABEL
Date: 20091116

ACTIVE INGREDIENTS: Oxygen 99 L/100 L

Oxygen